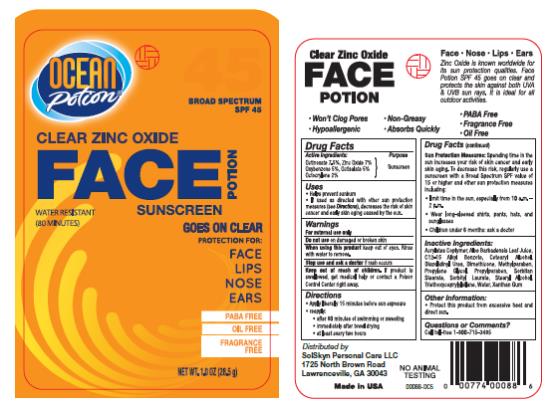 DRUG LABEL: OP spf45 Face Clear Zinc Potion
NDC: 70281-203 | Form: CREAM
Manufacturer: SolSkyn Personal Care LLC
Category: otc | Type: HUMAN OTC DRUG LABEL
Date: 20180215

ACTIVE INGREDIENTS: OCTINOXATE 7.5 g/100 g; ZINC OXIDE 7 g/100 g; OXYBENZONE 5 g/100 g; OCTISALATE 5 g/100 g; OCTOCRYLENE 2 g/100 g
INACTIVE INGREDIENTS: ALOE VERA LEAF; ALKYL (C12-15) BENZOATE; CETOSTEARYL ALCOHOL; DIAZOLIDINYL UREA; DIMETHICONE; METHYLPARABEN; PROPYLENE GLYCOL; PROPYLPARABEN; SORBITAN MONOSTEARATE; SORBITYL LAURATE; STEARYL ALCOHOL; TRIETHOXYCAPRYLYLSILANE; WATER; XANTHAN GUM

OP Face 45 Zinc

OP spf45 1oz Face Clear Zinc Potion

Active Ingredients

Octinoxate 7.5%

Active Ingredients

Zinc Oxide 7.0%

Active Ingredients

Oxybenzone 5.0%

Active Ingredients

Octisalate 5.0%

Active Ingredients

Octocrylene 2.0%

Purpose

Sunscreen

Uses:

- Helps prevent sunburn
- If used as directed with other sun protection measures (see Directions), decreases the risk of skin cancer and early skin aging caused by the sun.

Warnings:

For external use only

Keep out of reach of children.

If product is swallowed, get medical help or contact a Poison Control Center right away.

Directions:

- Apply liberally 15 minutes before sun exposure.
- Re-apply:
  • after 80 minutes of swimming or sweating
  • immediately after towel drying
  • at least every two hours
- Sun Protection Measures: Spending time in the sun increases your risk of skin cancer and early skin aging. To decrease this risk, regularly use a sunscreen with a Broad Spectrum SPF value of 15 or higher and other sun protection measures including:
  • limit time in the sun, especially from 10 a.m.-2 p.m.
  • wear long-sleeved shirts, pants, hats and sunglasses
  • Children under 6 months: ask a doctor.

Inactive Ingredients

Acrylates Copolymer, Aloe Barbadensis Leaf Juice, C12-15 Alkyl Benzote, Cetearyl Alcohol, Diazolidinyl Urea, Dimethicone, Methylparaben, Propylene Glycol, Propylparaben, Sorbitan Stearate, Sorbityl Laurate, Stearyl Alcohol, Triethoxycaprylylsilane, Water, Xanthan Gum

Other Information

- Protect this product from excessive heat and direct sun.

Questions or comments?

Call toll free 1-800-715-3485

PRINCIPAL DISPLAY PANEL

Clear Zinc Oxide
Face Potion
sunscreen
Net WT. 1.0 OZ (28.5 g)